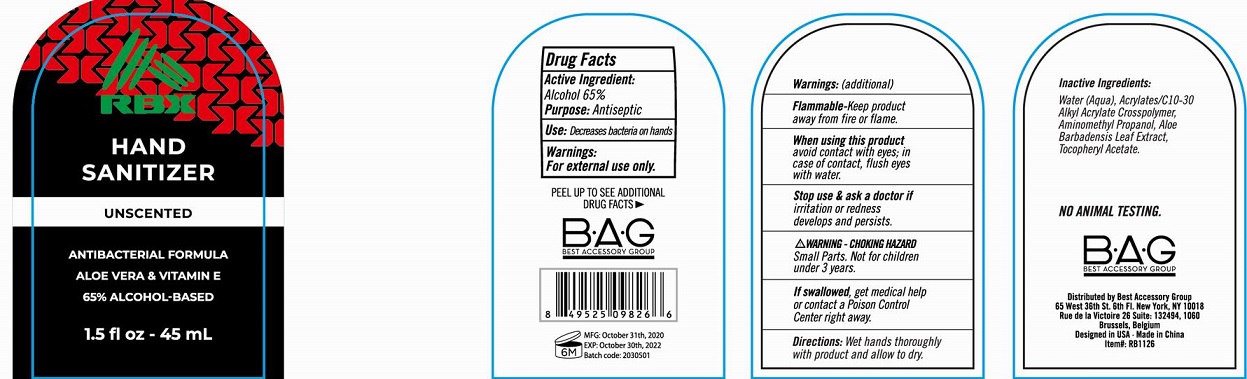 DRUG LABEL: RBX Hand Sanitizer Unscented
NDC: 56136-464 | Form: GEL
Manufacturer: Ganzhou Olivee Cosmetic Co., Ltd.
Category: otc | Type: HUMAN OTC DRUG LABEL
Date: 20201103

ACTIVE INGREDIENTS: ALCOHOL 65 mL/100 mL
INACTIVE INGREDIENTS: WATER; CARBOMER COPOLYMER TYPE A; AMINOMETHYLPROPANOL; .ALPHA.-TOCOPHEROL ACETATE, D-

HAND SANITIZER

Active ingredient

Alcohol 65%

Purpose

Antiseptic

Use

Decrease bacteria on hands.

Warnings

For external use only.

Flammable. Keep product away from fire or flame.

When using this product

avoid contact with eyes; in case of contact, flush eyes with water.

Stop use and ask a doctor if

irritation or redness develops and persists.

Keep out of reach of children.

If swallowed, get medical help or contact a Poison Control Center right away.

Directions

Wet hands thoroughly with product and allow to dry.

Inactive ingredients

Water (Aqua), ACRYLATES/C10-30 ALKYL ACRYLATE CROSSCOPOLYMER, AMINOMETHYL PROPANOL, Aloe Barbadensis Leaf Extract, Tocopheryl Acetate.

Warning - Choking Hazard

Small parts. Not for children under 3 years.

No Animal Testing.